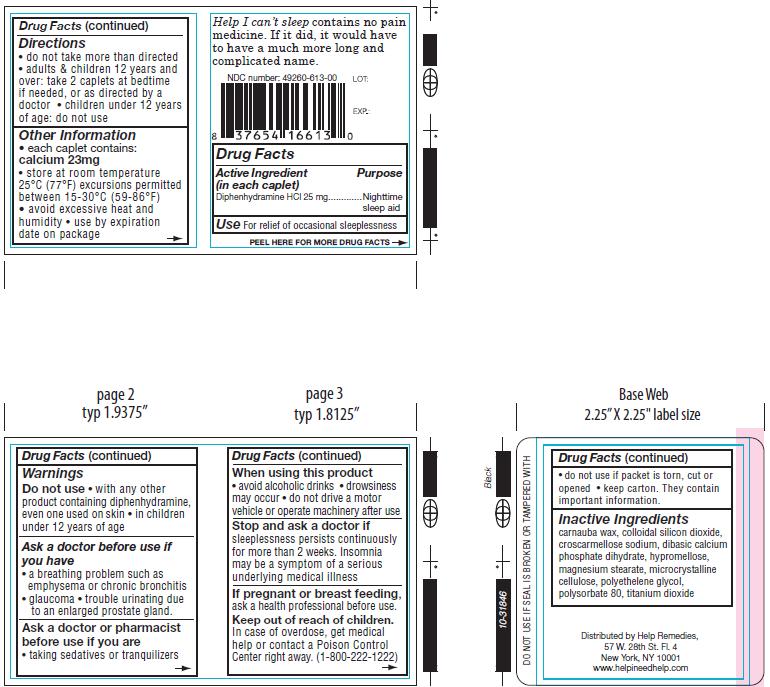 DRUG LABEL: Help I cant Sleep
NDC: 49260-613 | Form: TABLET
Manufacturer: Help Remedies, Inc. 
Category: otc | Type: HUMAN OTC DRUG LABEL
Date: 20110711

ACTIVE INGREDIENTS: DIPHENHYDRAMINE HYDROCHLORIDE 25 mg/1 1
INACTIVE INGREDIENTS: CARNAUBA WAX; SILICON DIOXIDE; CROSCARMELLOSE SODIUM; DIBASIC CALCIUM PHOSPHATE DIHYDRATE; HYPROMELLOSES; MAGNESIUM STEARATE; CELLULOSE, MICROCRYSTALLINE; POLYSORBATE 80; TITANIUM DIOXIDE; POLYETHYLENE GLYCOL

Drug Facts

Active Ingredient...................................................Purpose
(in each caplet)

Diphenhydramine HCl 25 mg...................................Nighttime/sleep aid

PURPOSE

Use: For relief of occasional sleeplessness

Warnings

- Ask a doctor before use if you have • a breathing problem such as emphysema or chronic bronchitis • glaucoma • trouble urinating due to an enlarged prostate gland.

- Ask a doctor or pharmacist before use if you are • taking sedatives or tranquilizers.

- When using this product:
• avoid alcoholic drinks • drowsiness may occur • do not drive a motor vehicle or operate machinery after use.

- Stop and ask a doctor if sleeplessness persists continuously for more than 2 weeks. Insomnia may be a symptom of a serious
underlying medical illness

Do not use

• with any other product containing diphenhydramine, even one used on skin • in children under 12 years of age.

Keep out of reach of children.
In case of overdose, get medical help or contact a Poison Control Center right away. (1-800-222-1222)

PREGNANCY OR BREAST FEEDING

If pregnant or breast feeding, ask a health professional before use.

Directions
• do not take more than directed
• adults and children 12 years and over: take 2 caplets at bedtime if needed, or as directed by a doctor
• children under 12 years of age: do not use

Other Information
• each caplet contains: calcium 23mg.
• store at room temperature 25°C (77°F) excursions permitted between 15-30°C (59-86°F)
• avoid excessive heat and humidity .
• use by expiration date on package.
• do not use if packet is torn, cut or opened.
• keep carton. They contain important information.

Inactive Ingredients
carnauba wax, colloidal silicon dioxide, croscarmellose sodium, dibasic calcium
phosphate dihydrate, hypromellose, magnesium stearate, microcrystalline cellulose,
polyethelene glycol, polysorbate 80, titanium dioxide.

QUESTIONS

Distributed by Help Remedies,
57 W. 28th St. Fl. 4
New York, NY 10001
www.helpineedhelp.com